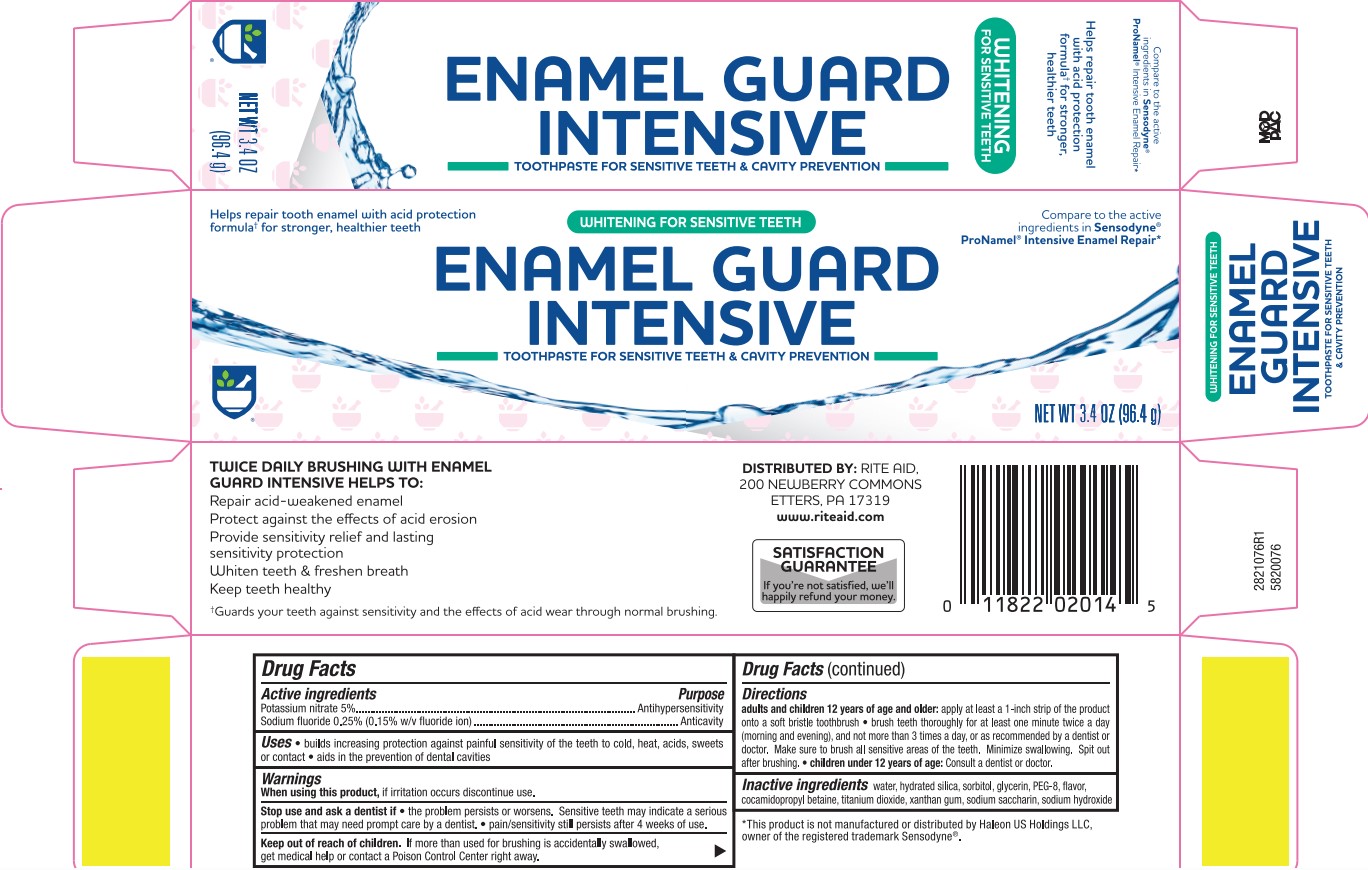 DRUG LABEL: Pronamel Repair Whitening
NDC: 11822-6310 | Form: PASTE, DENTIFRICE
Manufacturer: Rite Aid
Category: otc | Type: HUMAN OTC DRUG LABEL
Date: 20251121

ACTIVE INGREDIENTS: SODIUM FLUORIDE 0.15 g/100 g; POTASSIUM NITRATE 5 g/100 g
INACTIVE INGREDIENTS: POLYETHYLENE GLYCOL 400; TITANIUM DIOXIDE; XANTHAN GUM; SACCHARIN SODIUM; SODIUM HYDROXIDE; COCAMIDOPROPYL BETAINE; GLYCERIN; SORBITOL; WATER; HYDRATED SILICA

5820076 Rite Aid Enamel Guard Intensive (8015074)

ACTIVE INGREDIENT

Potassium nitrate 5% .................................................. Antihypersensitivity

Sodium fluoride 0.25% (0.15% w/v fluoride ion).......... Anticavity

When using this product, if irritation occurs discontinue use.

Stop use and ask a dentist if the problem persists or worsens.

Sensitive teeth may indicate a serious problem that may need prompt care by a dentist. pain/sensitivity stil persists after 4 weeks of use.

PURPOSE

Anthihypersensitivity

Anticavity

INDICATIONS AND USAGE

builds increasing protection against painful sensitivty of the teeth to cold, acids, sweets, or contact. Aids in the prevention of dental cavities.

KEEP OUT OF REACH OF CHILDREN

If more than used for brushing is accidentaly swallowed, get medical help or contact a Posion Control Center right away.

DOSAGE AND ADMINISTRATION

adults and children 12 years of age and older: apply at least a 1-inch strip of the product ontp a soft bristle toothbrush. Brush teeth thoroughly for at least one minute twice a day (morning and evening), and not more than 3 times a day, or as recommended by a dentist or doctor. make sure to brush all sensitive areas of the teeth. Minimize swallowing. Spit out after brushing.

children under 12 years of age: Consult a dentist or doctor.

INACTIVE INGREDIENT

water, hydrated silica, sorbitol, glycerin, PEG-8, flavor, cocamidopropyl betaine, titanium dioxide, xanthan gum, sodium saccharin, sodium hydroxide